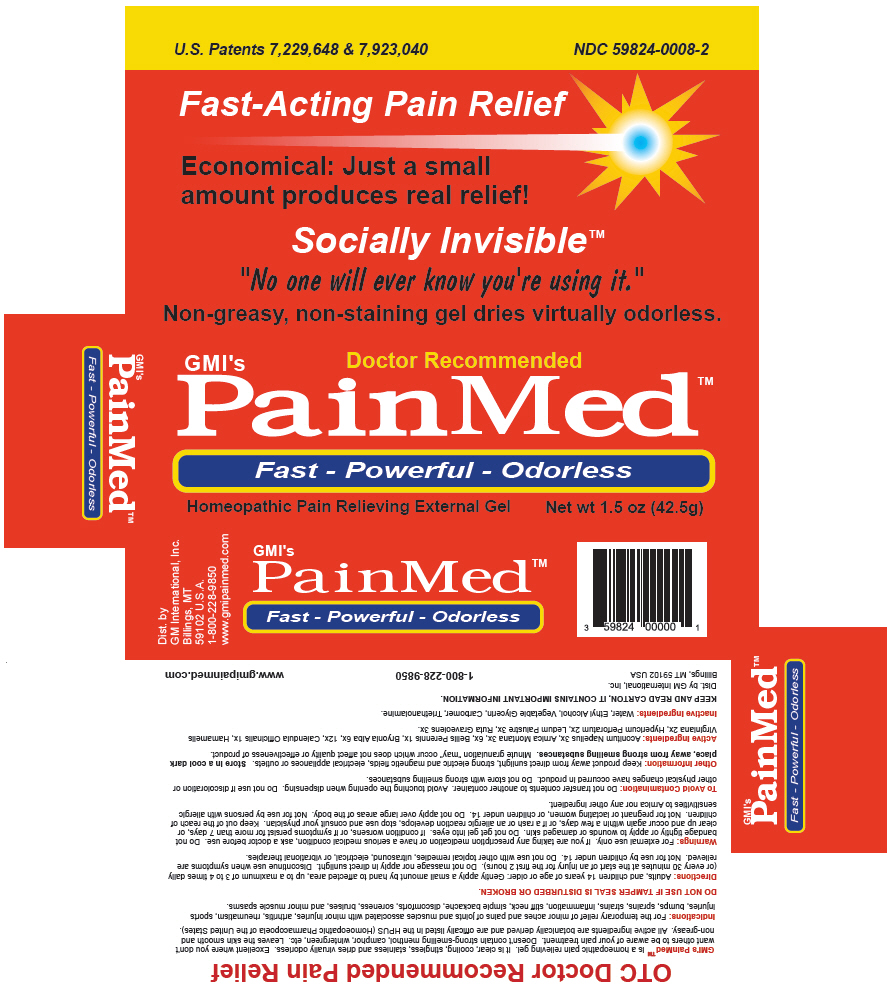 DRUG LABEL: PainMed 
NDC: 59824-0008 | Form: GEL
Manufacturer: G M International, Inc.
Category: homeopathic | Type: HUMAN OTC DRUG LABEL
Date: 20171227

ACTIVE INGREDIENTS: ACONITUM NAPELLUS 3 [hp_X]/1 g; ARNICA MONTANA 6 [hp_X]/1 g; BELLIS PERENNIS 1 [hp_X]/1 g; BRYONIA ALBA ROOT 12 [hp_X]/1 g; CALENDULA OFFICINALIS FLOWERING TOP 1 [hp_X]/1 g; HAMAMELIS VIRGINIANA ROOT BARK/STEM BARK 2 [hp_X]/1 g; HYPERICUM PERFORATUM 2 [hp_X]/1 g; RHODODENDRON TOMENTOSUM LEAFY TWIG 3 [hp_X]/1 g; RUTA GRAVEOLENS FLOWERING TOP 3 [hp_X]/1 g
INACTIVE INGREDIENTS: WATER; ALCOHOL; GLYCERIN; CARBOMER HOMOPOLYMER TYPE C (ALLYL PENTAERYTHRITOL CROSSLINKED); TROLAMINE

PainMed™
Homeopathic Pain Relieving External

Indications

PURPOSE

For the temporary relief of minor aches and pains of joints and muscles associated with minor injuries, arthritis, rheumatism, sports injuries, bumps, sprains, strains, inflammation, stiff neck, simple backache, discomforts, soreness, bruises, and minor muscle spasms.

DO NOT USE IF TAMPER SEAL IS DISTURBED OR BROKEN.

Directions

Adults, and children 14 years of age or older: Gently apply a small amount by hand to affected area, up to a maximum of 3 to 4 times daily (or every 30 minutes at the start of an injury for the first 2 hours). Do not massage nor apply in direct sunlight. Discontinue use when symptoms are relieved. Not for use by children under 14. Do not use with other topical remedies, ultrasound, electrical, or vibrational therapies.

Warnings

For external use only.

ASK DOCTOR

If you are taking any prescription medication or have a serious medical condition, ask a doctor before use.

DO NOT USE

Do not bandage tightly or apply to wounds or damaged skin. Do not get gel into eyes.

ASK DOCTOR/PHARMACIST

If condition worsens, or if symptoms persist for more than 7 days, or clear up and occur again within a few days, or if a rash or an allergic reaction develops, stop use and consult your physician.

Keep out of the reach of children.

PREGNANCY OR BREAST FEEDING

Not for pregnant or lactating women, or children under 14.

DO NOT USE

Do not apply over large areas of the body. Not for use by persons with allergic sensitivities to Arnica nor any other ingredient.

Active Ingredients

Aconitum Napellus 3x, Arnica Montana 3x, 6x, Bellis Perennis 1x, Bryonia Alba 6x, 12x, Calendula Officinalis 1x, Hamamelis Virginiana 2x, Hypericum Perforatum 2x, Ledum Palustre 3x, Ruta Graveolens 3x.

Inactive Ingredients

Water, Ethyl Alcohol, Vegetable Glycerin, Carbomer, Triethanolamine

KEEP AND READ CARTON, IT CONTAINS IMPORTANT INFORMATION.

Dist. by GM International, Inc.
Billings, MT 59102 USA

QUESTIONS

1-800-228-9850

www.gmipainmed.com

PRINCIPAL DISPLAY PANEL - 42.5g Tube Carton

GMI's
Doctor Recommended

PainMed™

Fast - Powerful - Odorless

Homeopathic Pain Relieving External Gel
Net wt 1.5 oz (42.5g)